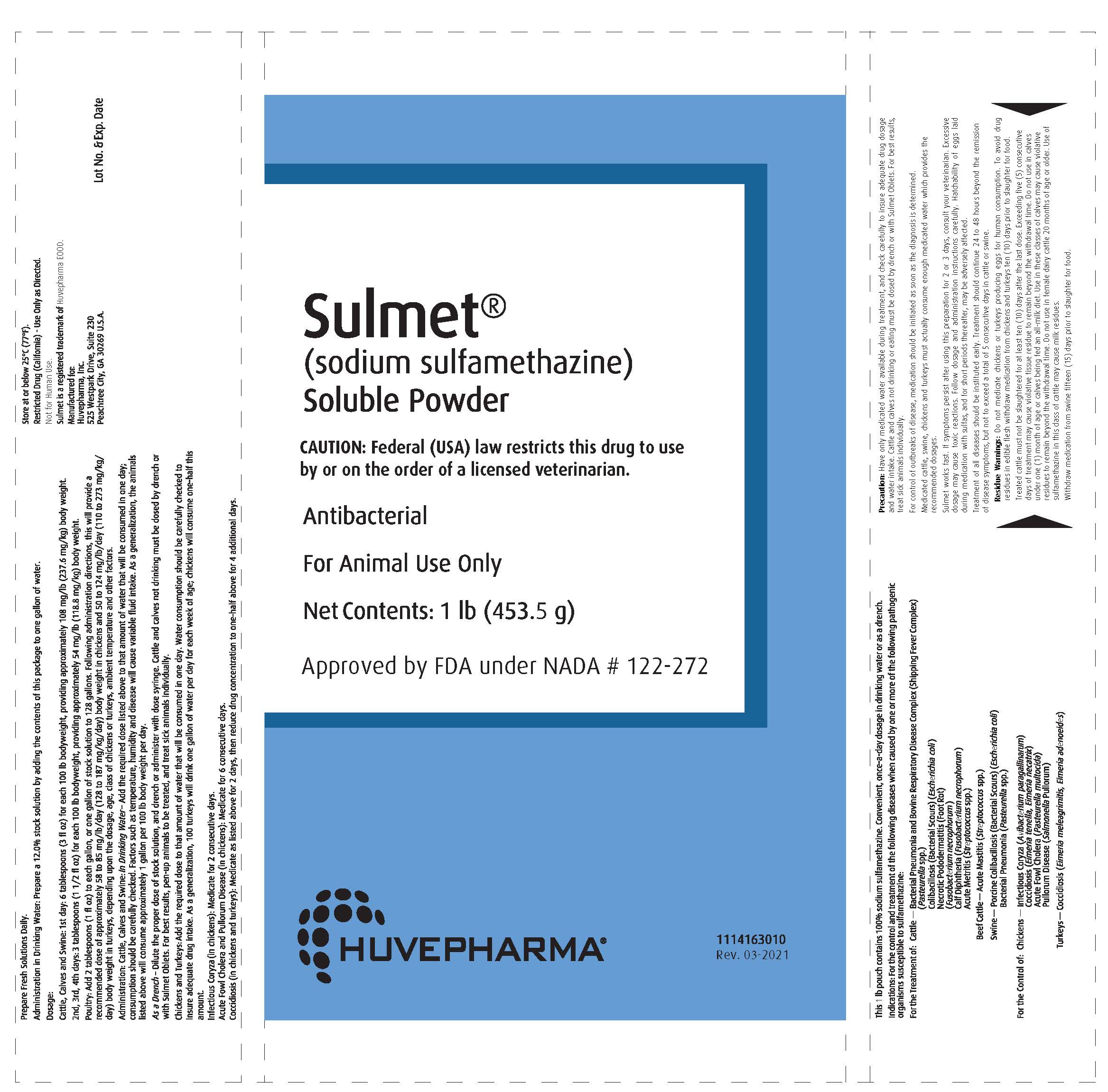 DRUG LABEL: Sulmet
NDC: 23243-6500 | Form: POWDER, FOR SOLUTION
Manufacturer: Huvepharma, Inc.
Category: animal | Type: PRESCRIPTION ANIMAL DRUG LABEL
Date: 20210915

ACTIVE INGREDIENTS: SULFAMETHAZINE SODIUM 453.51 g/453.51 g

Sulmet® Soluble Powder

Front Panel

Sulmet®

(sodium sulfamethazine)
Soluble Powder

CAUTION: Federal (USA) law restricts this drug to use by or on the order of a licensed veterinarian.

Antibacterial

For Animal Use Only

Net Contents: 1 lb (453.5 g)

Approved by FDA under NADA # 122-272

Huvepharma®

1114163010
Rev. 03-2021

Side Panel

Restricted Drug (California) - Use Only as Directed.
Not for Human Use.
Sulmet is a registered trademark of Huvepharma EOOD.

Manufactured for:
Huvepharma, Inc.
525 Westpark Drive, Suite 230
Peachtree City, GA 30269 U.S.A.

Lot No. & Exp. Date

VETERINARY INDICATIONS

This 1 lb pouch contains 100% sodium sulfamethazine. Convenient, once-a-day dosage in drinking water or as a drench.

Indications: For the control and treatment of the following diseases when casused by one or more of the following pathogenic organisms susceptible to sulfamethazine.

For the treatment of: Cattle - Bacterial Pneumonia and Bovine Respiratory Disease Complex (Shipping Fever Complex)

(Pasteurella spp.)
Colibacillosis (Bacterial Scours)(Escherichia coli)

Necrotic Pododermatitis (Foot Rot)

(Fusobacterium necrophorum)

Calf Diptheria (Fusobacterium necrophorum)

Acute Metritis (Streptococcus spp.)

Beef Cattle-Acute Mastitis (Streptococcus spp.)

Swine-Porcine Colibacillosis (Bacterial Scours)(Escherichia coli)
Bacterial Pneumonia (Pasteurella spp.)

For the Control of: Chickens- Infectious Coryza (Avibacterium paragallinarum)
Coccidiosis (Eimeria tenella, Eimeria necatrix)
Acute Fowl Cholera (Pasteurella multocida)
Pullorum Disease (Salmonella Pullorum)

Turkeys- Coccidiosis (Eimeria meleagrimitis, Eimeria adenoeides)

Precaution:

Have only medicated water available during treatment, and check carefully to insure adequate drug dosage
and water intake. Cattle and calves not drinking or eating must be dosed by drench or with Sulmet Oblets. For best results,
treat sick animals individually.

For control of outbreaks of disease, medication should be initiated as soon as the diagnosis is determined.

Medicated cattle, swine, chickens and turkeys must actually consume enough medicated water which provides the
recommended dosages.

Sulmet works fast. If symptoms persist after using this preparation for 2 or 3 days, consult your veterinarian. Excessive
dosage may cause toxic reactions. Follow dosage and administration instructions carefully. Hatchability of eggs laid
during medication with sulfas, and for short periods thereafter, may be adversely affected.

Treatment of all diseases should be instituted early. Treatment should continue 24 to 48 hours beyond the remission
of disease symptoms, but not to exceed a total of 5 consecutive days in cattle or swine.

Residue Warnings:

Do not medicate chickens or turkeys producing eggs for human consumption. To avoid drug
residues in edible flesh withdraw medication from chickens and turkeys ten (10) days prior to slaughter for food.

Treated cattle must not be slaughtered for at least ten (10) days after the last dose. Exceeding five (5) consecutive
days of treatment may cause violative tissue residue to remain beyond the withdrawal time. Do not use in calves
under one (1) month of age or calves being fed an all-milk diet. Use in these classes of calves may cause violative
residues to remain beyond the withdrawal time. Do not use in female dairy cattle 20 months of age or older. Use of
sulfamethazine in this class of cattle may cause milk residues.

Withdraw medication from swine fifteen (15) days prior to slaughter for food.

Administration in Drinking Water

Prepare fresh Solutions Daily

Administration in Drinking Water: Prepare a 12.0% stock solution by adding the contents of this package to one gallon of water.

Dosage:

Cattle, Calves and Swine: 1st day: 6 tablespoons (3 fl oz) for each 100 lb bodyweight, providing approximately 108 mg/lb (237.6 mg/kg) body weight.

2nd, 3rd, 4th days: 3 tablespoons (1 1/2 fl oz) for each 100 lb bodyweight, providing approximately 54 mg/lb (118.8 mg/kg) body weight.

Poultry: Add 2 tablespoons (1 fl oz) to each gallon, or one gallon of stock solution to 128 gallons. Following administration directions, this will provide a recommended dose of approximately 58 to 85 mg/lb/day (128 to 187 mg/kg/day) body weight in chickens and 50 to 124 mg/lb/day (110 to 273 mg/kg/day) body weight in turkeys, depending on the dosage, age, class of chickens or turkeys, ambient temperature and other factors.

Administration: Cattle, Calves and Swine: In Drinking Water-Add the required dose listed above to that amount of water that will be consumed in one day; consumption should be carefully checked. Factors such as temperature, humidity and disease will cause variable fluid intake. As a generalization, the animals listed above will consume approximately 1 gallon per 100 lb body weight per day.

As a Drench-Dilute the proper dose of stock solution, and drench or administer with dose syringe. Cattle and calves not drinking must be dosed by drench or with Sulmet Oblets. For best results, pen-up animals to be treated, and treat sick animals individually.

Chickens and Turkeys: Add the required dose to the that amount of water that will be consumed in one day. Water consumption should be carefully checked to insure adequate intake. As a generalization, 100 turkeys will drink one gallon of water per day for each week of age; chickens will consume one-half this amount.

Infectious Coryza (in chickens): Medicate for 2 consecutive days.

Acute Fowl Cholera and Pullorum Disease (in chickens): Medicate for 6 consecutive days.

Coccidiosis (in chickens and turkeys): Medicate as listed above for 2 days, then reduce drug concentration to one-half above for 4 additional days.

Storage

Store at or below 25°C (77°F)